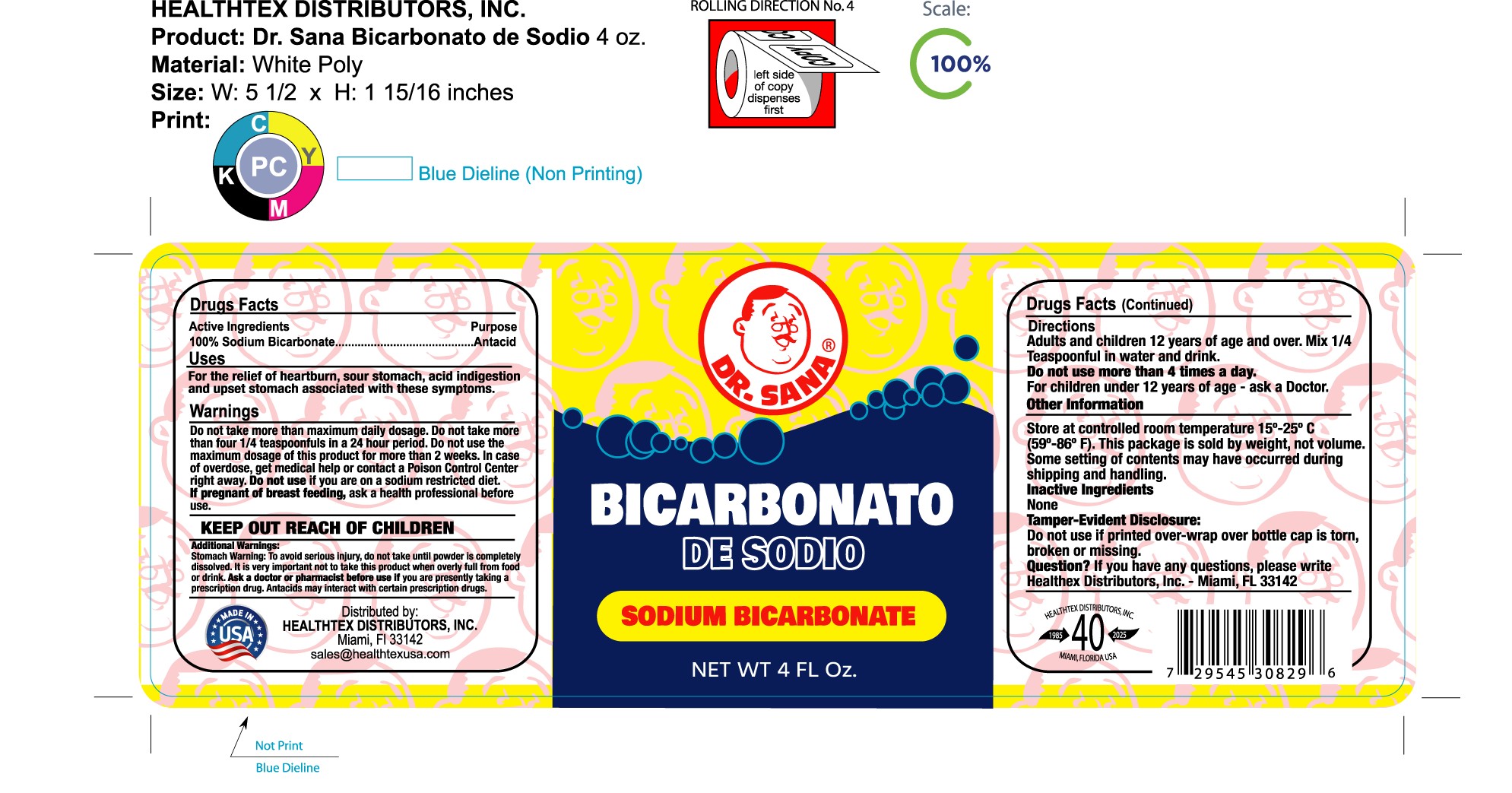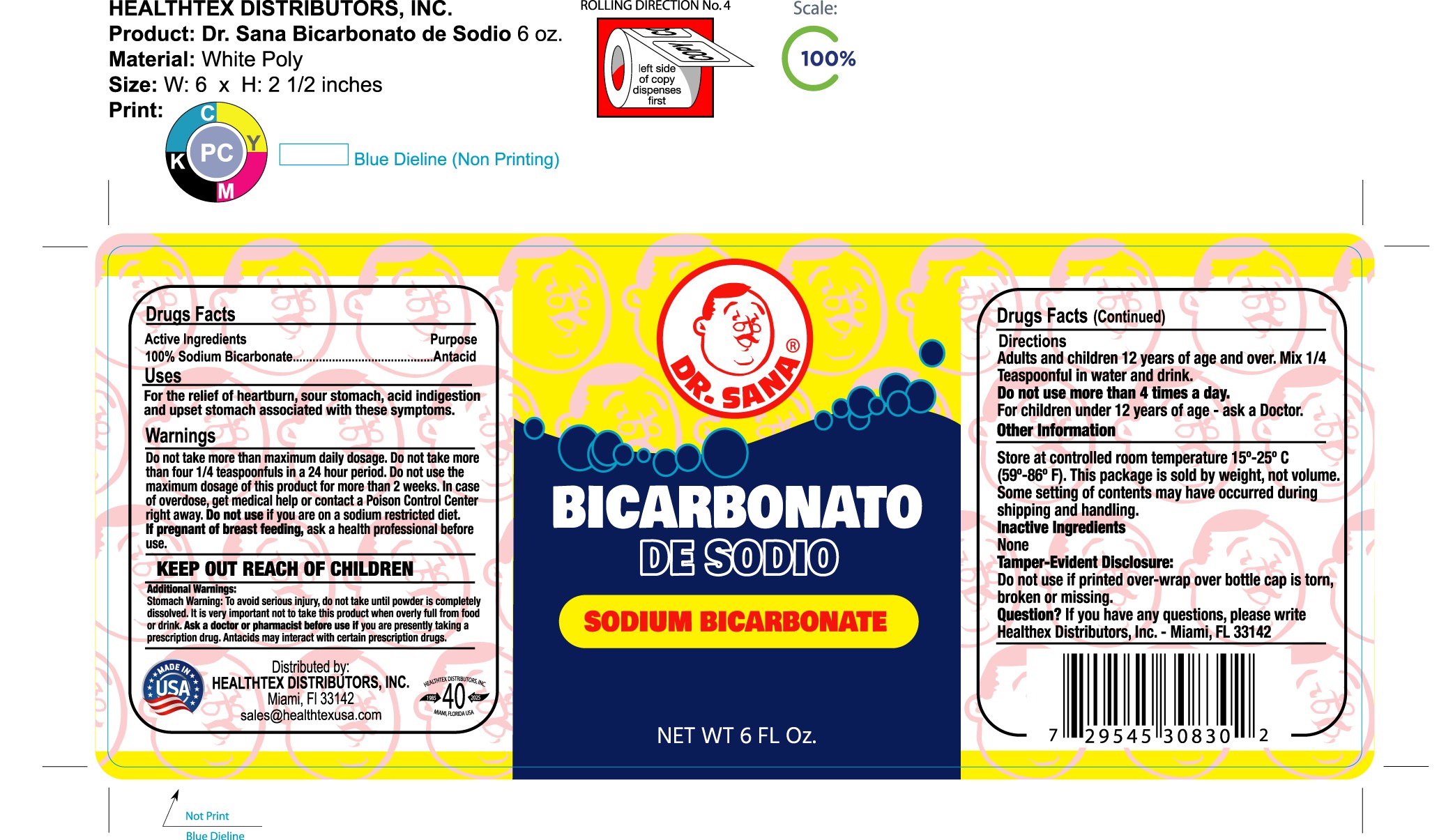 DRUG LABEL: DR. SANA BICARBONATO DE SODIO
NDC: 84178-050 | Form: POWDER
Manufacturer: Evi Labs
Category: otc | Type: HUMAN OTC DRUG LABEL
Date: 20260107

ACTIVE INGREDIENTS: SODIUM BICARBONATE 315 mg/1 g

DR. SANA BICARBONATO DE SODIO 4 OZ AND 6 OZ

Purpose

Antacid

Uses

For the relief of heartburn, sour stomach, acid indigestion, and upset stomach associated with this sintomas.

Warnings

Do not take more maximum daily dosage. Do not take more than four 1/4 teaspoonfuls in 24 hour period. Do not use the maximum dosage of this product for more than 2 weeks. In case of overdose, get medical help or contact a Poison Control Center right away. Do not use if you are on a sodium restricte diet. If pregnant or breastfeeding, ask a health professional before use.

KEEP OUT OF REACH OF CHILDREN

Additional warning:

Stomach warning: To avoid serious injury, do not take until the powder is completely dissolved. It is very important not to take this product when overly full from food or drink. Ask the doctor or pharmacist before use if you are presently taking a prescription drug. Antacids may interact with certain prescription drugs.

Directions

Adults and children 12 years of age and over. Mix 1/4 teaspoonful in water and drink.
Do not use more than 4 times a day.
For children under 12 years of age - ask a Doctor.

Other Information

Store at controlled room temperature 15-25°C (59-86 °F). This package is sold by weight, not volume. Some settings of the contents may have occurred during shipping and handling.

Inactive Ingredients

None.

Tamper-Evident Disclosure

Do not use if the printed over-wrap over the bottle cap is torn, broken, or missing.

Questions? If you have any questions, please write Healthtx Distributor, Inc, Miami, Fl 33142.

Inactive Ingredient

none